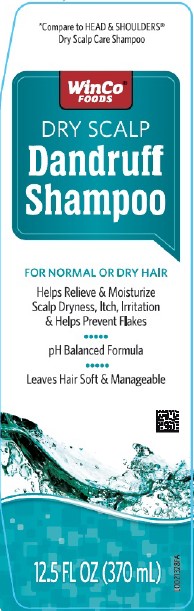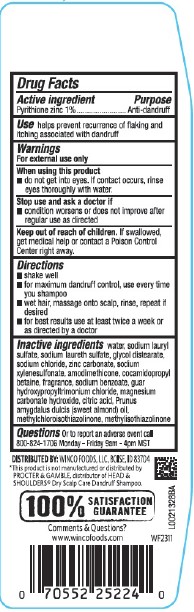 DRUG LABEL: Dry Scalp
NDC: 67091-179 | Form: SHAMPOO
Manufacturer: WinCo Foods, LLC
Category: otc | Type: HUMAN OTC DRUG LABEL
Date: 20260212

ACTIVE INGREDIENTS: PYRITHIONE ZINC 10 mg/1 mL
INACTIVE INGREDIENTS: WATER; SODIUM LAURYL SULFATE; SODIUM LAURETH SULFATE; GLYCOL DISTEARATE; SODIUM CHLORIDE; ZINC CARBONATE; SODIUM XYLENESULFONATE; AMODIMETHICONE (800 CST); COCAMIDOPROPYL BETAINE; SODIUM BENZOATE; GUAR HYDROXYPROPYLTRIMONIUM CHLORIDE (1.7 SUBSTITUENTS PER SACCHARIDE); MAGNESIUM CARBONATE HYDROXIDE; CITRIC ACID MONOHYDRATE; ALMOND OIL; METHYLCHLOROISOTHIAZOLINONE; METHYLISOTHIAZOLINONE

WinCo 281.007/281AN
Dandruff Shampoo, Dry Scalp

Active ingredient

Pyrithione zinc 1%

Purpose

Anti-dandruff

Use

Helps prevent recurrence of flaking and itching associated with dandruff

Warnings

For external use only

When using this product

- do not get into eyes. If contact occurs, rinse eyes thoroughly with water.

Stop use and ask a doctor if

- condition worsens or does not improve after regular use as directed

Keep out of reach of children

If swallowed, get medical help or contact a Poison Control Center right away.

Directions

- shake well
- for maximum dandruff control, use every time you shampoo
- wet hair, massage onto scalp, rinse, repeat if desired
- for best results use at least twice a week or as directed by a doctor

inactive ingredients

water, sodium lauryl sulfate, sodium laureth sulfate, glycol distearate, sodium chloride, zinc carbonate, sodium xylenesulfonate, amodimethicone, cocamidopropyl betaine, fragrance, sodium benzoate, guar hydroxypropyltrimonium chloride, magnesium carbonate hydroxide, citric acid, prunus amygdalus dulcis (sweet almond) oil, methylchloroisothiazolinone, methylisothiazolinone

questions

Or to report an adverse even call 800-824-1706 Monday - Friday 9am - 4pm MST

Adverse Reactions

DISTRIBUTED BY: WINCO FOODS, LLC BOISE, ID 83704

100% SATISFACTION GUARANTEE

Comments & Questions?

www.wincofoods.com

Disclaimer

*This product is not manufactured or distributed by PROCTOR & GAMBLE, distributor of HEAD & SHOULDERS® Dry Scalp Care Dandruff Shampoo.

Principal display panel

*Compare to HEAD & SHOULDERS®Dry Scalp Care Shampoo

WinCo®FOODS

DRY SCALP

Dandruff Shampoo

FOR NORMAL OR DRY HAIR

Helps Relieve & Moisturize

Scalp Dryness, Itch, Irritation

& Helps Prevent Flakes

pH Balanced Formula

Leaves Hair Soft & Manageable

12.5 FL OZ (370 mL)